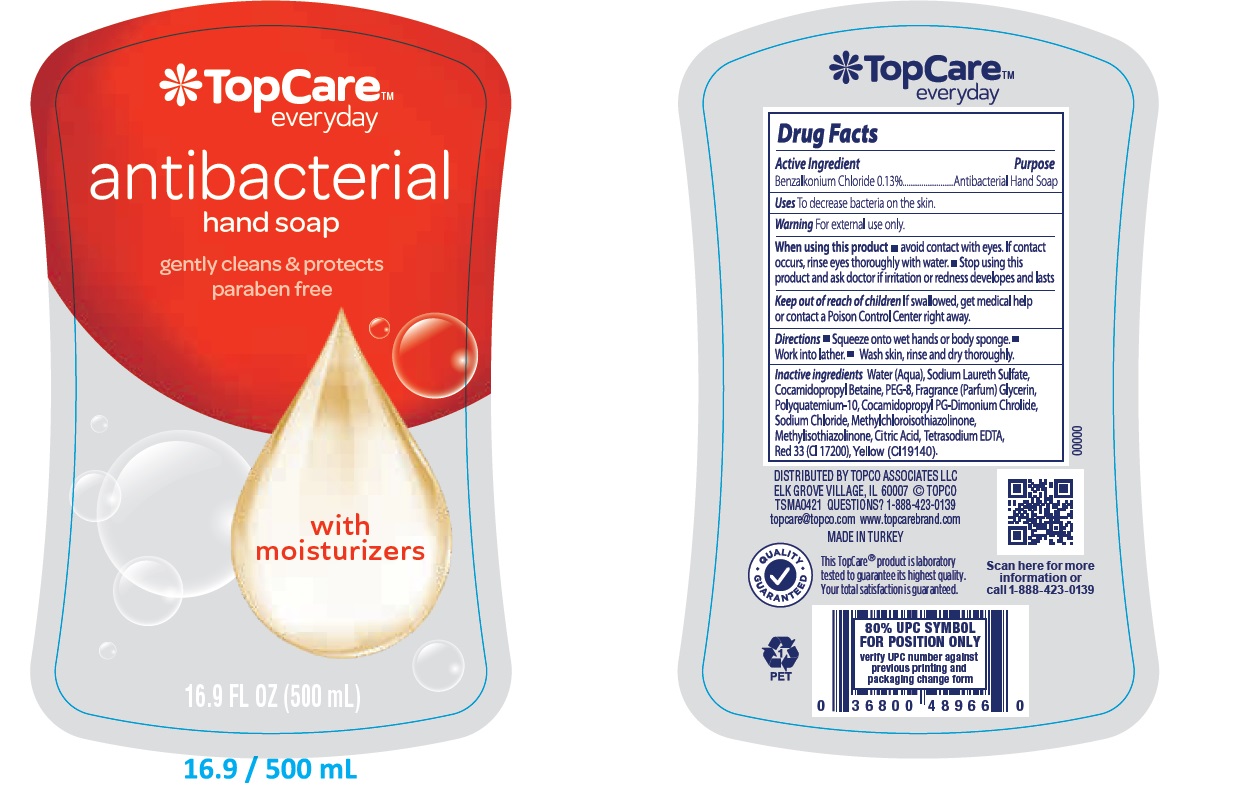 DRUG LABEL: Antibacterial
NDC: 76772-033 | Form: LIQUID
Manufacturer: TSM ITHALAT IHRACAT SANAYI VE DIS TICARET LIMITED SIRKETI
Category: otc | Type: HUMAN OTC DRUG LABEL
Date: 20210719

ACTIVE INGREDIENTS: BENZALKONIUM CHLORIDE 1.3 g/1 mL
INACTIVE INGREDIENTS: WATER; SODIUM LAURETH SULFATE; COCAMIDOPROPYL BETAINE; POLYQUATERNIUM-10 (1000 MPA.S AT 2%); SODIUM CHLORIDE; METHYLISOTHIAZOLINONE; GLYCERIN; COCAMIDOPROPYL PG-DIMONIUM CHLORIDE; METHYLCHLOROISOTHIAZOLINONE; CITRIC ACID ACETATE; EDETIC ACID; D&C RED NO. 33

Top Care Antibacterial Liquid Hand Soap - With Moisturizer

Active ingredients

Benzalkonium chloride 0.13%.................Anitbacterial Hand soap

Purpose

Antibacterial Hand Soap

Use

for handwashing to decrease bacteria on the skin

Warnings

For external use only: hands only

When using this product

- avoid contact with eyes. If contact occurs, rinse eyes with water

Stop use and ask a doctor if

- irritation or redness develops
- condition persists for more than 72 hours

Keep out of reach of children

If swallowed, get medical help or contact a Poison Control Center right away

Directions

- Squeeze onto wet hands or body sponge
- Work into lather
- Wash skin,rinse and dry toroughly

INACTIVE INGREDIENT

water, sodium laureth sulfate , cocamidopropyl betaine, sodium chloride, glycerin,

fragrance, polyquatemium-10 , PEG-8 , citric acid, tetrasodium EDTA, cocamidopropyl pg-dimonium chrolide,

methylchloroisothiazolinone, methlisothiazolinone, Yellow (CI 19140),Red 33